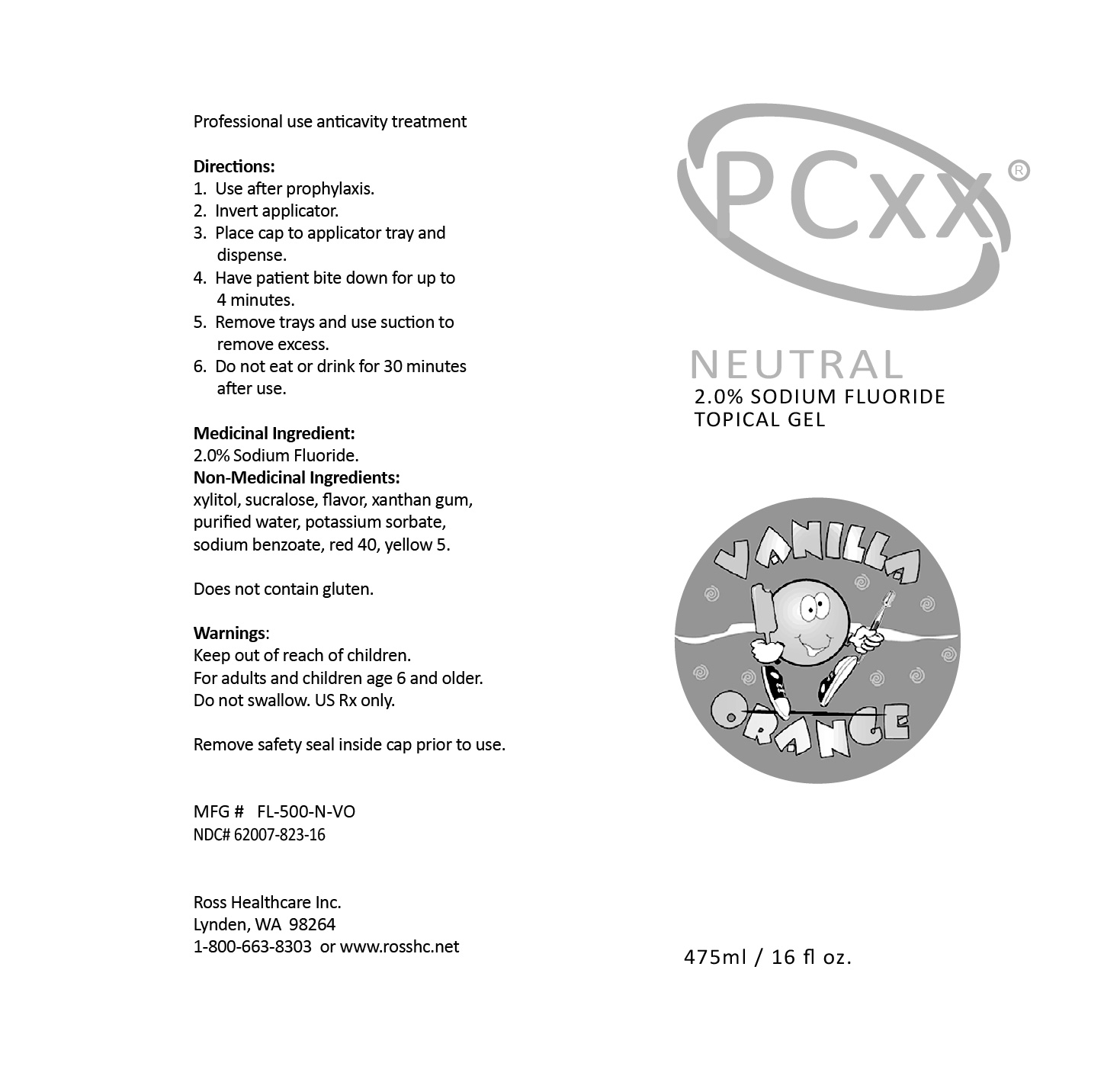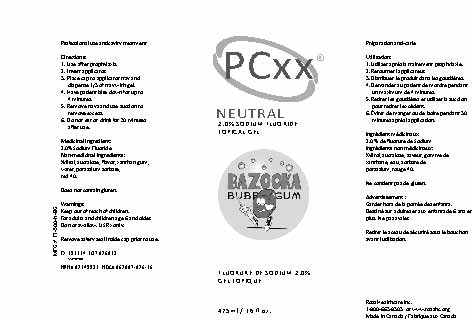 DRUG LABEL: PCXX VANILLA ORANGE NEUTRAL GL
NDC: 62007-823 | Form: GEL
Manufacturer: Ross Healthcare Inc.
Category: prescription | Type: HUMAN PRESCRIPTION DRUG LABEL
Date: 20251106

ACTIVE INGREDIENTS: SODIUM FLUORIDE 20 mg/1 mL

PCXX VANILLA ORANGE NEUTRAL GEL

DOSAGE AND ADMINISTRATION

Shake well before use. This is a one minute or four minute fluoride gel for in-office patient use. It is normally used as a preventative caries treatment two times a year.

1. After thorough prophylaxsis, fill two single or one dual tray, one third full with gel. Air dry teeth and insert trays into the mouth.

2. Instruct patient to bite down lightly but firmly for one minute (80% effectiveness) or four minutes (100% effectiveness).

3. Remove trays. Instruct patient to expectorate any excess gel and not to eat or drink for at least 30 minute